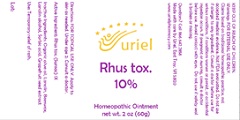 DRUG LABEL: Rhus tox. 10%
NDC: 48951-8369 | Form: OINTMENT
Manufacturer: Uriel Pharmacy Inc.
Category: homeopathic | Type: HUMAN OTC DRUG LABEL
Date: 20201222

ACTIVE INGREDIENTS: TOXICODENDRON PUBESCENS LEAF 1 [hp_X]/1 g
INACTIVE INGREDIENTS: OLIVE OIL; LANOLIN; YELLOW WAX; CITRUS PARADISI SEED; SORBIC ACID; LANOLIN ALCOHOLS

Rhus tox. 10%

INDICATIONS AND USAGE

Directions: FOR TOPICAL USE ONLY.

DOSAGE AND ADMINISTRATION

Apply to skin as needed. Under age 2: Consult a doctor.

Active Ingredient: Rhus tox. (Sumac) 1X

INACTIVE INGREDIENT

Inactive Ingredients: Organic olive oil, Lanolin, Beeswax, Lanolin alcohol, Sorbic acid, Grapefruit seed extract

PURPOSE

Use: Temporary relief of rash.

KEEP OUT OF REACH OF CHILDREN.

Warnings: FOR EXTERNAL USE ONLY.
Claims based on traditional homeopathic practice, not accepted medical evidence. Not FDA evaluated. Do not use if allergic to any ingredient. Consult a doctor before use for serious conditions, if conditions worsen or persist, or accidental ingestion occurs. If pregnant or nursing, consult a doctor before use. Avoid contact with eyes. Do not use if safety seal is broken or missing.

Questions? Call 866.642.2858
Made with care by Uriel, East Troy, WI 53120
www.urielpharmacy.com

Lot: